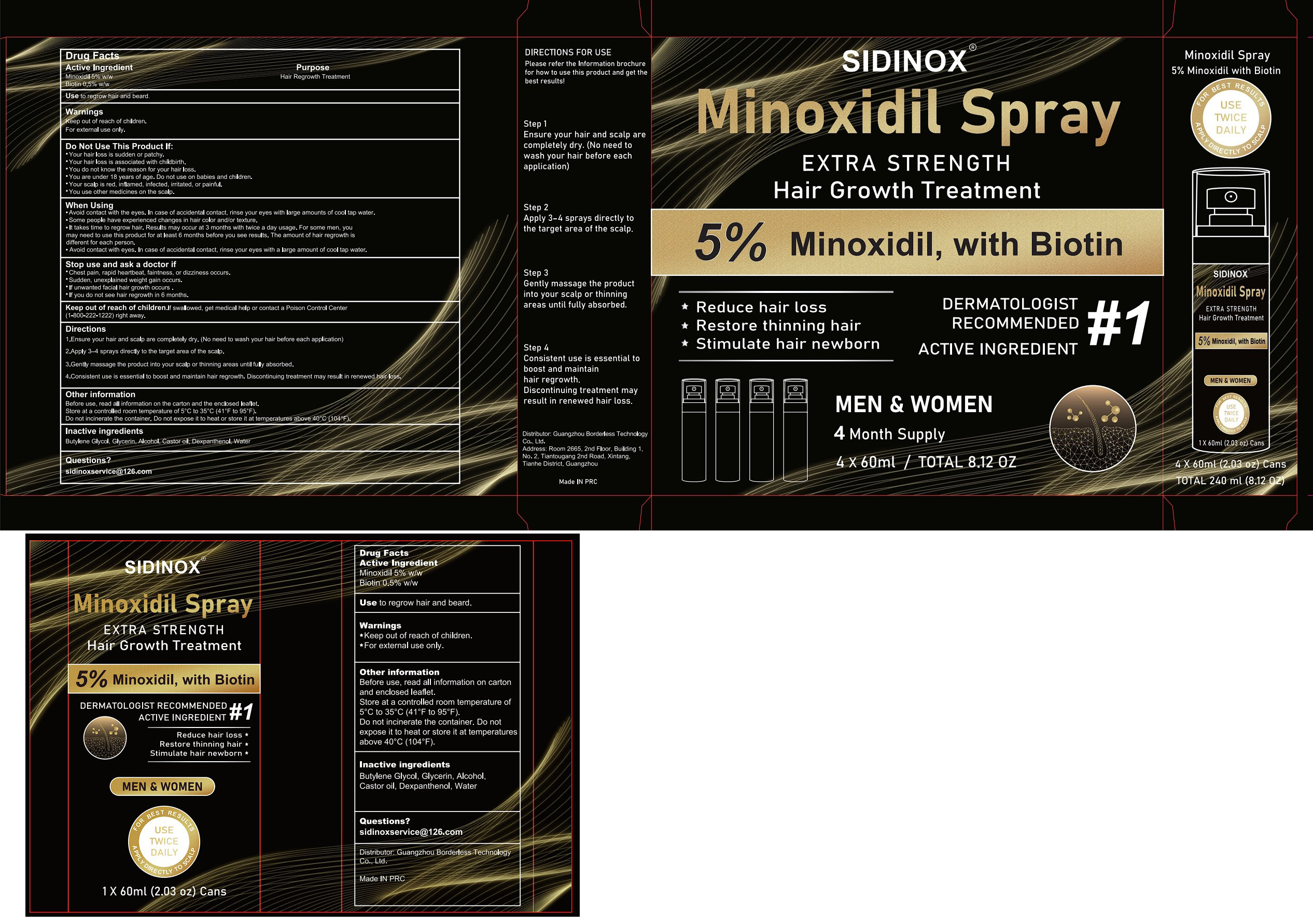 DRUG LABEL: Sidinox 5% Minoxidil Hair Growth Sprays Serum
NDC: 85304-007 | Form: LIQUID
Manufacturer: Guangzhou Borderless Technology Co., Ltd.
Category: otc | Type: HUMAN OTC DRUG LABEL
Date: 20250603

ACTIVE INGREDIENTS: BIOTIN 0.5 g/100 mL; MINOXIDIL 5 g/100 mL
INACTIVE INGREDIENTS: BUTYLENE GLYCOL; ALCOHOL; DEXPANTHENOL; WATER; CASTOR OIL; GLYCERIN

85304-007 Sidinox 5% Minoxidil Hair Growth Sprays Serum

ACTIVE INGREDIENT

Minoxidil 5%
Biotin 0.5%

PURPOSE

Hair Regrowth Treatment

INDICATIONS AND USAGE

Use to regrow hair and beard

Keep out of reach of children.
For external use only.

DO NOT USE

Your hair loss is sudden or patchy.
Your hair loss is associated with childbirth.
You do not know the reason for your hair loss.
You are under 18 years of age. Do not use on babies and children.
Your scalp is red, inflamed, infected, irritated, or painful.
You use other medicines on the scalp.

WHEN USING

Avoid contact with the eyes. In case of accidental contact, rinse your eyes with large amounts of cool lap water.
Some people have experienced changes in hair color and/or texture.
lt takes time to regrow hair. Results may occur at 3 months with twice a day usage. For some men, youmay need to use this product for at least 6 months before you see results, The amount of hair regrowth isdifferent for each person.
Avoid contact with eyes. ln case of accidental contact, rinse your eyes with a large amount of cool tap water.

STOP USE

Chest pain, rapid heartbeat, faintness, or dizziness occurs.
Sudden, unexplained weight gain occurs.
lf unwanted facial hair growth occurs .
lf you do not see hair regrowth in 6 months.

Keep out of reach of children.lf swalowed, get medical help or contact a Poison Control Center
11-800-222-1222)right away.

DOSAGE AND ADMINISTRATION

1.Ensure your hair and scalp are completely dry. (No need to wash your hair before eachapplication
2.Apply 3 4 sprays directly to the target area of the scalp.
3.Gently massage the product into your scalp or thinning areas until fully absorbed.
4.Consistent use is essentlal to boost and maintain hair regrowth. Discontinuing treatment may result in renewed hair loss

INACTIVE INGREDIENT

Butylene Glycol
Glycerin
Alcohol
Castor oil
Dexpanthenol
Water